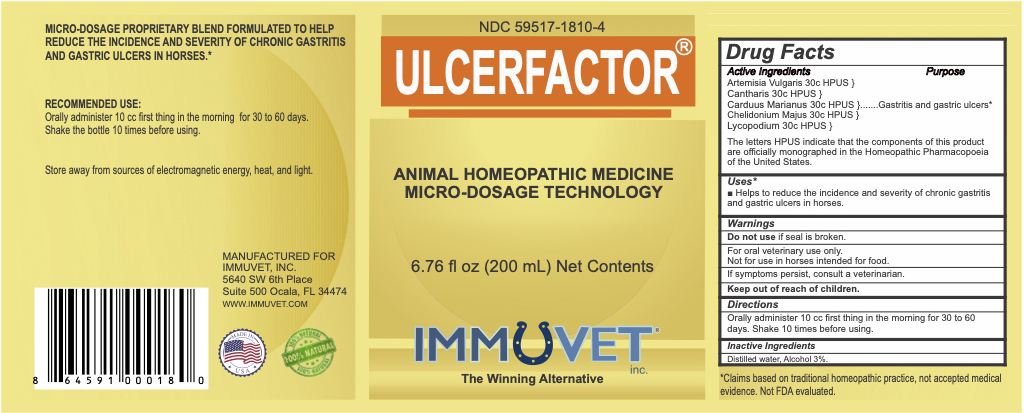 DRUG LABEL: ULCERFACTOR
NDC: 59517-1810 | Form: LIQUID
Manufacturer: Immuvet, Inc.
Category: homeopathic | Type: OTC ANIMAL DRUG LABEL
Date: 20251104

ACTIVE INGREDIENTS: ARTEMISIA VULGARIS ROOT 30 [hp_C]/1 mL; LYTTA VESICATORIA 30 [hp_C]/1 mL; MILK THISTLE 30 [hp_C]/1 mL; CHELIDONIUM MAJUS 30 [hp_C]/1 mL; LYCOPODIUM CLAVATUM SPORE 30 [hp_C]/1 mL
INACTIVE INGREDIENTS: ALCOHOL; WATER

ULCERFACTOR

PURPOSE

Helps to reduce the incidence and severity of chronic gastritis and gastric ulcers in horses.

DIRECTIONS

Orally administer 10 cc for the first 20 days, thereafter 10 cc every other day. Shake 10 times before using.

ACTIVE INGREDIENTS

Artemisia Vulgaris 30c HPUS
Cantharis 30c HPUS
Carduus Marianus 30c HPUS
Chelidonium Majus 30c HPUS
Lycopodium 30c HPUS

INACTIVE INGREDIENTS

Distilled water, Alcohol 3%

WARNINGS

Do not use if seal is broken.
For Oral Veterinary Use Only.
Not for use in Horses intended for food.
If problems persist, contact a veterinarian.
Keep out of reach of children.

OTHER INFORMATION

Claims based on traditional homeopathic practice, not accepted medical evidence. Not FDA evaluated.